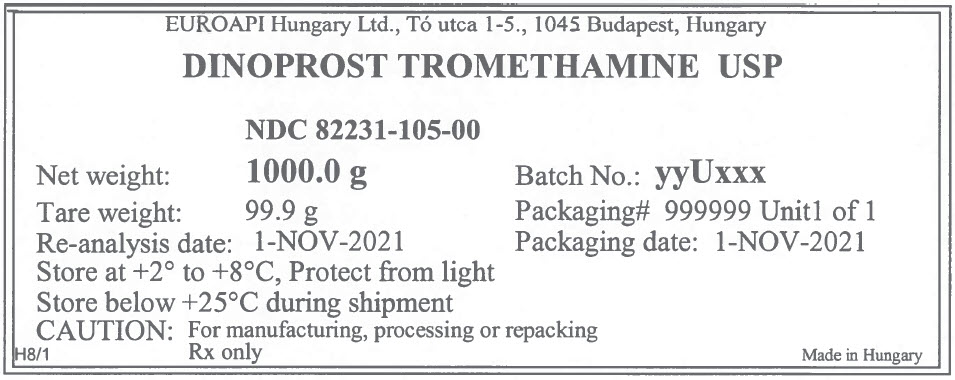 DRUG LABEL: Dinoprost Tromethamine
NDC: 82231-105 | Form: POWDER
Manufacturer: EUROAPI Hungary Ltd.
Category: other | Type: BULK INGREDIENT - ANIMAL DRUG
Date: 20220318

ACTIVE INGREDIENTS: Dinoprost Tromethamine 1 g/1 g

DINOPROST TROMETHAMINE USP

PRINCIPAL DISPLAY PANEL - Shipping Label

EUROAPI Hungary Ltd., Tó utca 1-5., 1045 Budapest, Hungary

DINOPROST TROMETHAMINE USP

NDC 82231-105-00

Net weight: 1000.0 g

Tare weight: 99.9 g

Re-analysis date: 1-NOV-2021

Batch No.: yyUxxx

Packaging# 999999 Unit1 of 1

Packaging date: 1-NOV-2021

Store at +2° to +8°C, Protect from light

Store below +25°C during shipment

CAUTION: For manufacturing, processing or repacking

H8/1

Rx only

Made in Hungary